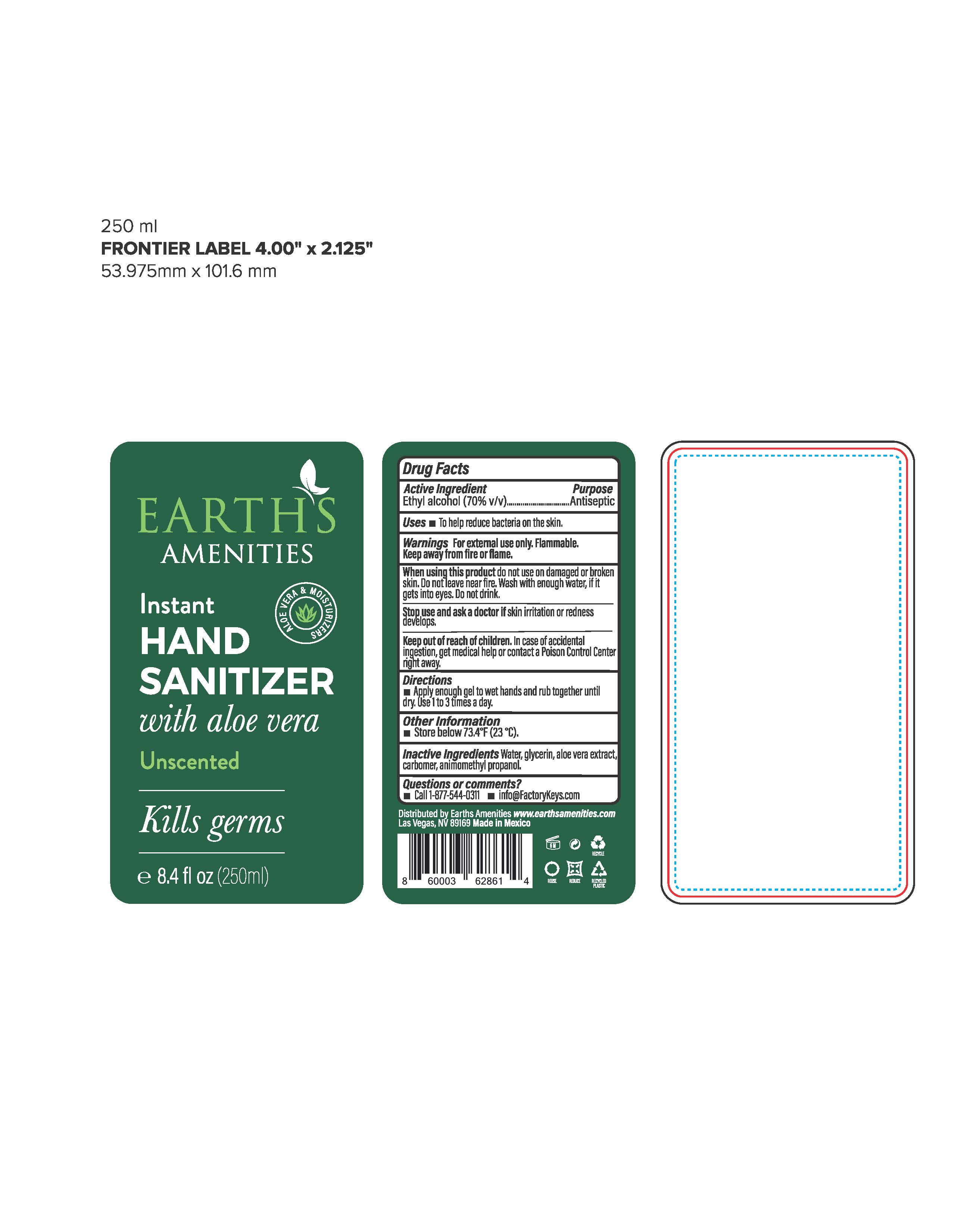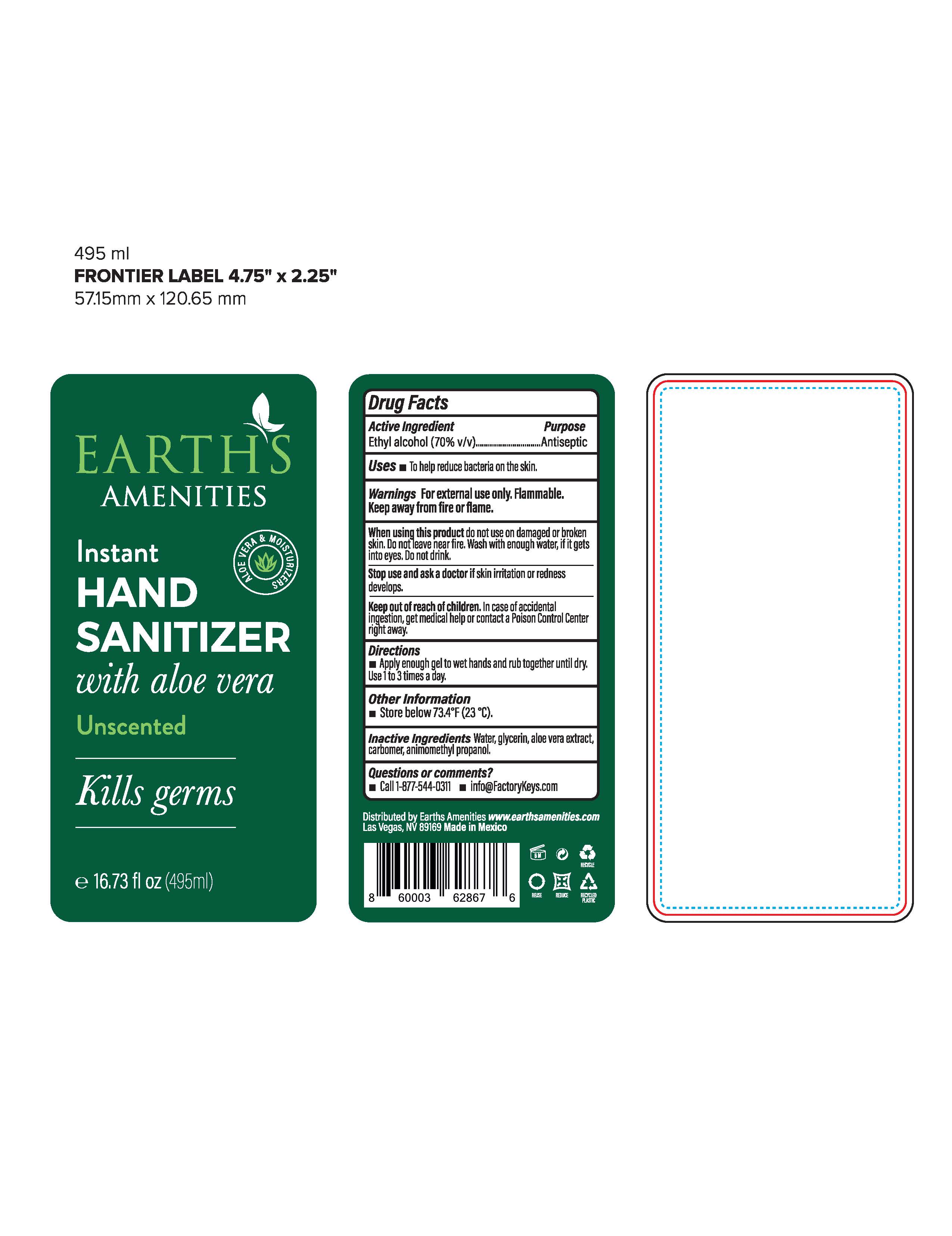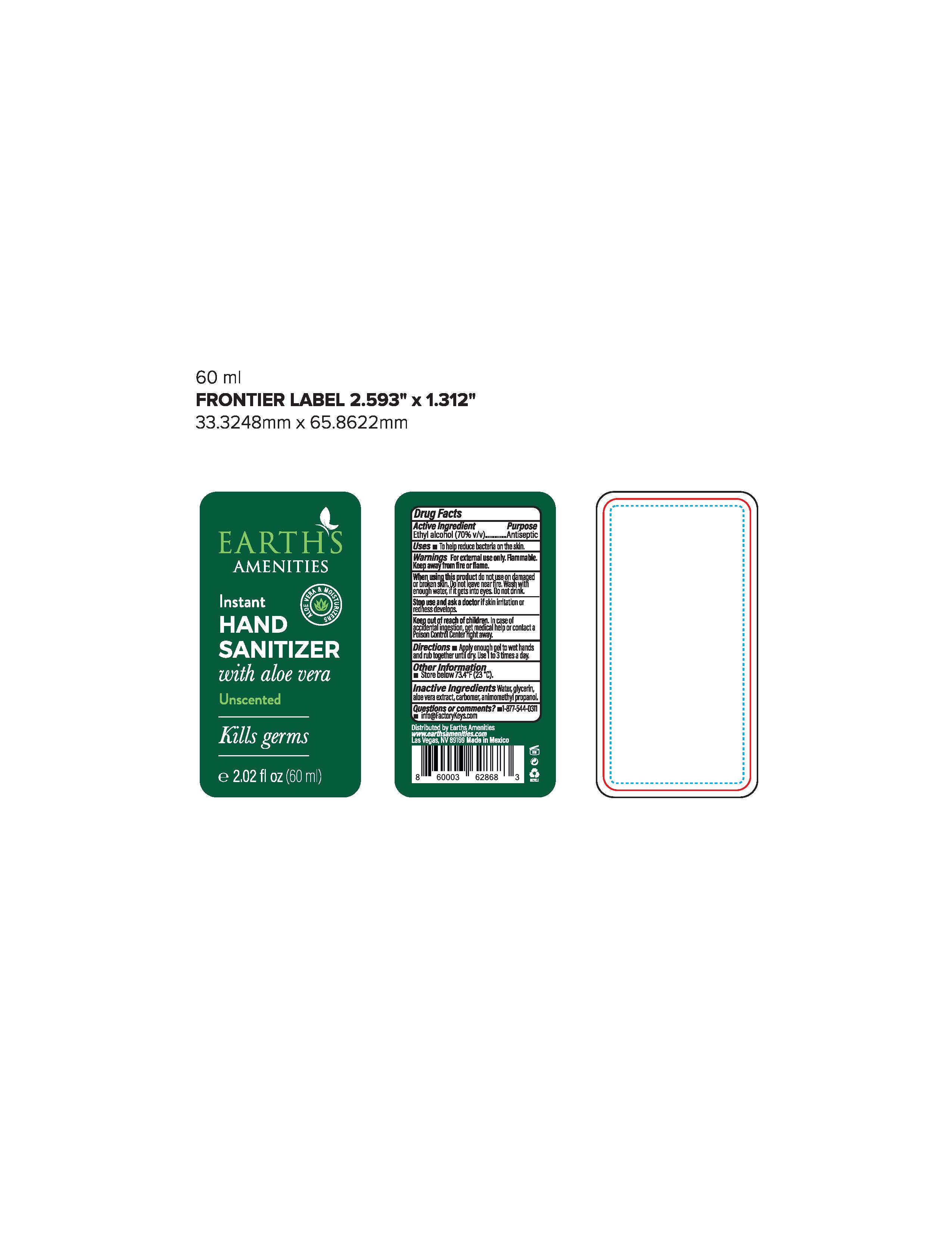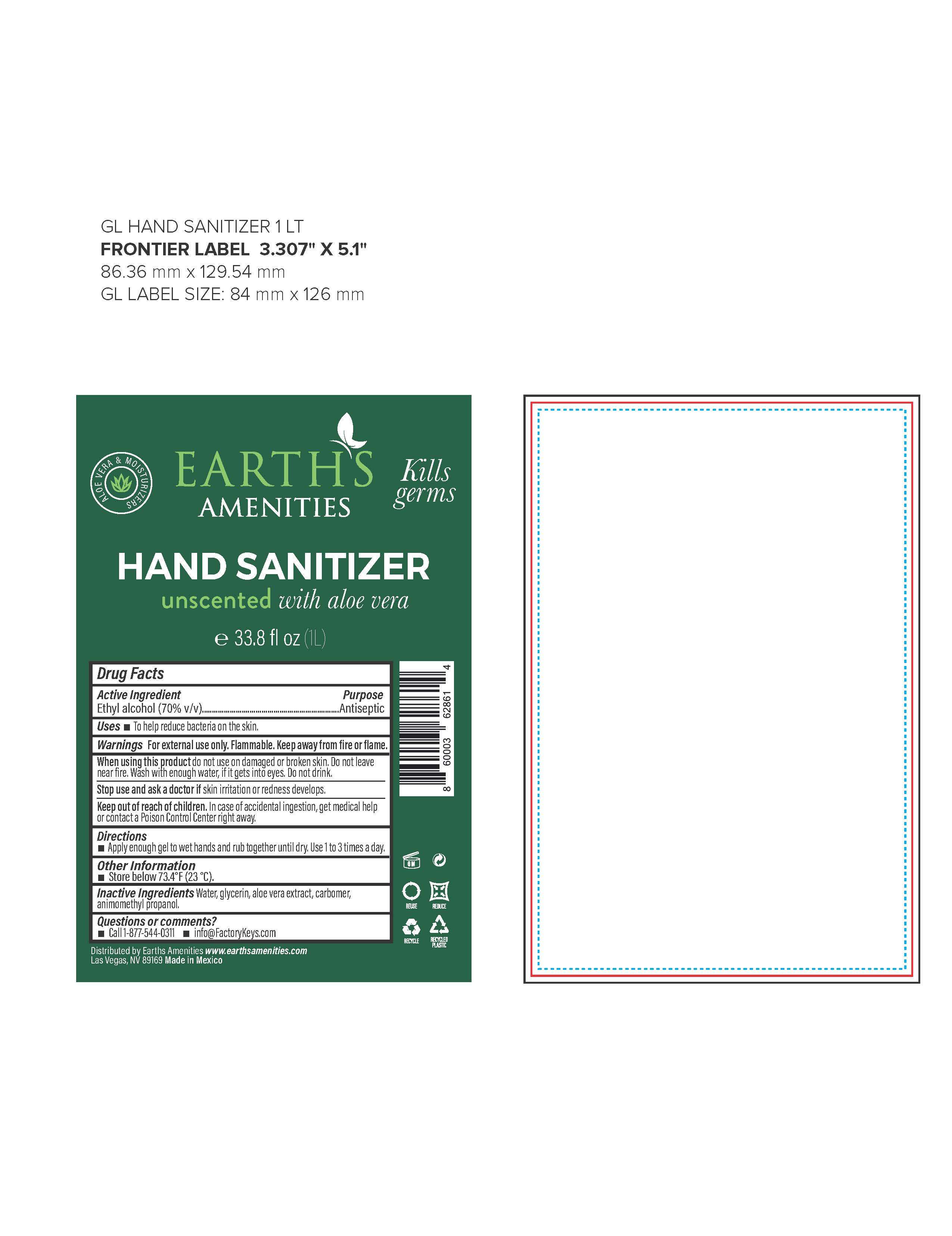 DRUG LABEL: Instant Hand Sanitizer
NDC: 74949-001 | Form: LIQUID
Manufacturer: Earths Amenities
Category: otc | Type: HUMAN OTC DRUG LABEL
Date: 20200427

ACTIVE INGREDIENTS: ALCOHOL 70 mL/100 mL
INACTIVE INGREDIENTS: AMINOMETHYLPROPANOL 1 mL/100 mL; ALOE VERA FLOWER 1 mL/100 mL; GLYCERIN 1 mL/100 mL; WATER 27 mL/100 mL; CARBOMER 940 1 mL/100 mL

This is a hand sanitizer manufactured according to the OTC Monograph Safety and Effectiveness of Consumer Antiseptic Rubs; Topical Antimicrobial Drug Products for Over-the-Counter Human Use.

The hand sanitizer is manufactured using

1. Alcohol (ethanol) (USP or Food Chemical Codex (FCC) grade) (70%, volume/volume (v/v)) in an aqueous solution denatured according to Alcohol and Tobacco Tax and Trade Bureau regulations in 27 CFR part 20.
2. Glycerin
3. Aloe Vera Extract
4. Water
5. Carbomer
6. Aminomethyl Propanol

Active Ingredient(s)

Alcohol 70% v/v. Purpose: Antiseptic

Purpose

Antiseptic, Hand Sanitizer

Use

To help reduce bacteria on the skin.

Warnings

For external use only. Flammable. Keep away from fire or flame

Do not use on damaged or broken skin. Do not leave near fire. Wash with enough water, if it gets into eyes. Do not drink.

Stop use and ask a doctor if skin irritation or redness develops.

KEEP OUT OF REACH OF CHILDREN

In case of accidental ingestion, get medical help or contact a Poison Control Center right away

Directions

Apply enough gel to wet hands and rub together until dry. Use 1 to 3 times a day.

Other information

Store below 73.4F (23C)

Inactive ingredients

Water, glycerin, aloe vera extract, carbomer, aminomethyl propanol

Package Label - Principal Display Panel

60 mL NDC: 74949-001-60

250 mL NDC: 74949-001-25

495 mL NDC: 74949-001-49

1L NDC: 74949-001-01